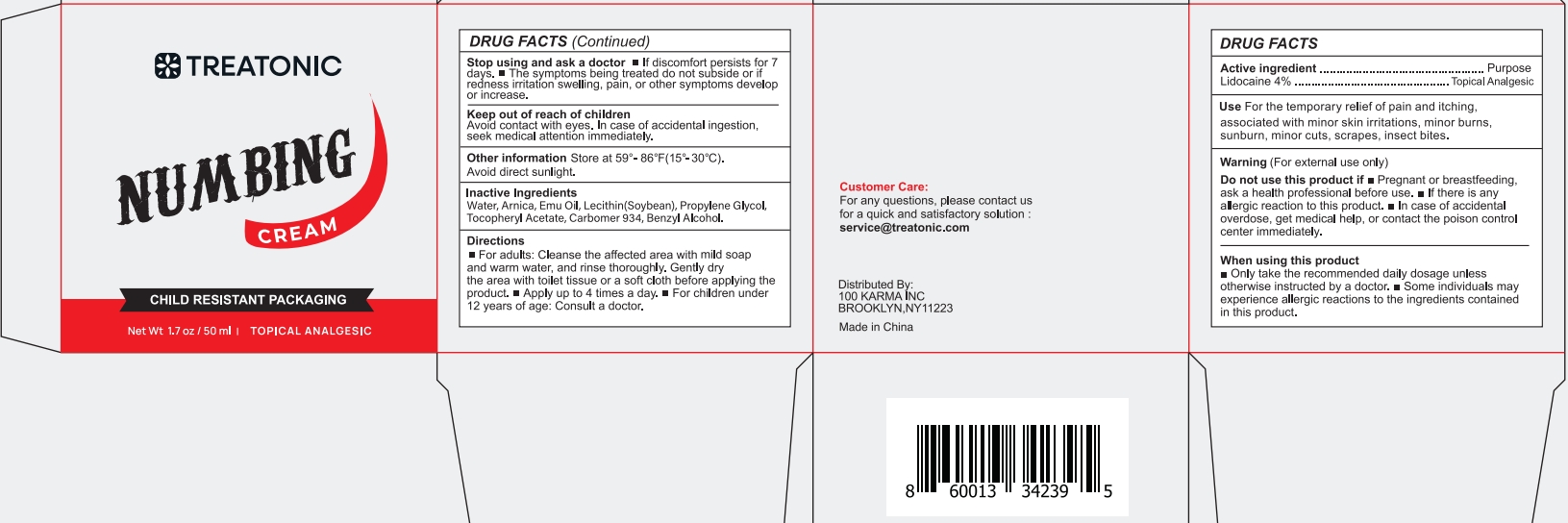 DRUG LABEL: Numbing Cream
NDC: 85569-002 | Form: CREAM
Manufacturer: 100 KARMA INC
Category: otc | Type: HUMAN OTC DRUG LABEL
Date: 20250520

ACTIVE INGREDIENTS: LIDOCAINE 4 mg/100 mL
INACTIVE INGREDIENTS: WATER; .ALPHA.-TOCOPHEROL ACETATE; EMU OIL; PROPYLENE GLYCOL; ARNICA MONTANA FLOWER; LECITHIN, SOYBEAN; BENZYL ALCOHOL; CARBOMER 934

Initial Drug Listing - 4% lidocaine numbing cream

ACTIVE INGREDIENT

4% lidocaine

PURPOSE

topical analgesic

INDICATIONS AND USAGE

For the temporary relief of pain and itching!associated with minor skin irritations, minor burnssunburn,minor cuts,scrapes, insect bites.

WARNINGS

For external use only

Do not use this product if

- Pregnant or breastfeeding, ask a health professional before use.
- If there is any allergic reaction to this product.
- In case of accidental overdose, get medical help, or contact the poison control center immediately.

WHEN USING

- Only take the recommended daily dosage unless otherwise instructed by a doctor.
- Some individuals may experience allergic reactions to the ingredients contained in this product.

Stop using and ask a doctor

- If discomfort persists for 7 days.
- The symptoms being treated do not subside or if redness irritation swelling, pain, or other symptoms develop or increase.

Keep out of reach of children Avoid contact with eyes.
In case of accidental ingestion, seek medical attention immediately.

DOSAGE AND ADMINISTRATION

- For adults: Cleanse the affected area with mild soap and warm water, and rinse thoroughly. Gently dry the area with toilet tissue or a soft cloth before applying the product.
- Apply up to 4 times a day.
- For children under 12 years of age: Consult a doctor.

OTHER SAFETY INFORMATION

Store at 59°-86°F (15°-30°C). Avoid direct sunlight.

INACTIVE INGREDIENT

Water, Arnica, Emu Oil, Lecithin(Soybean), Propylene Glycol,Tocopheryl Acetate, Carbomer 934, Benzyl Alcohol.